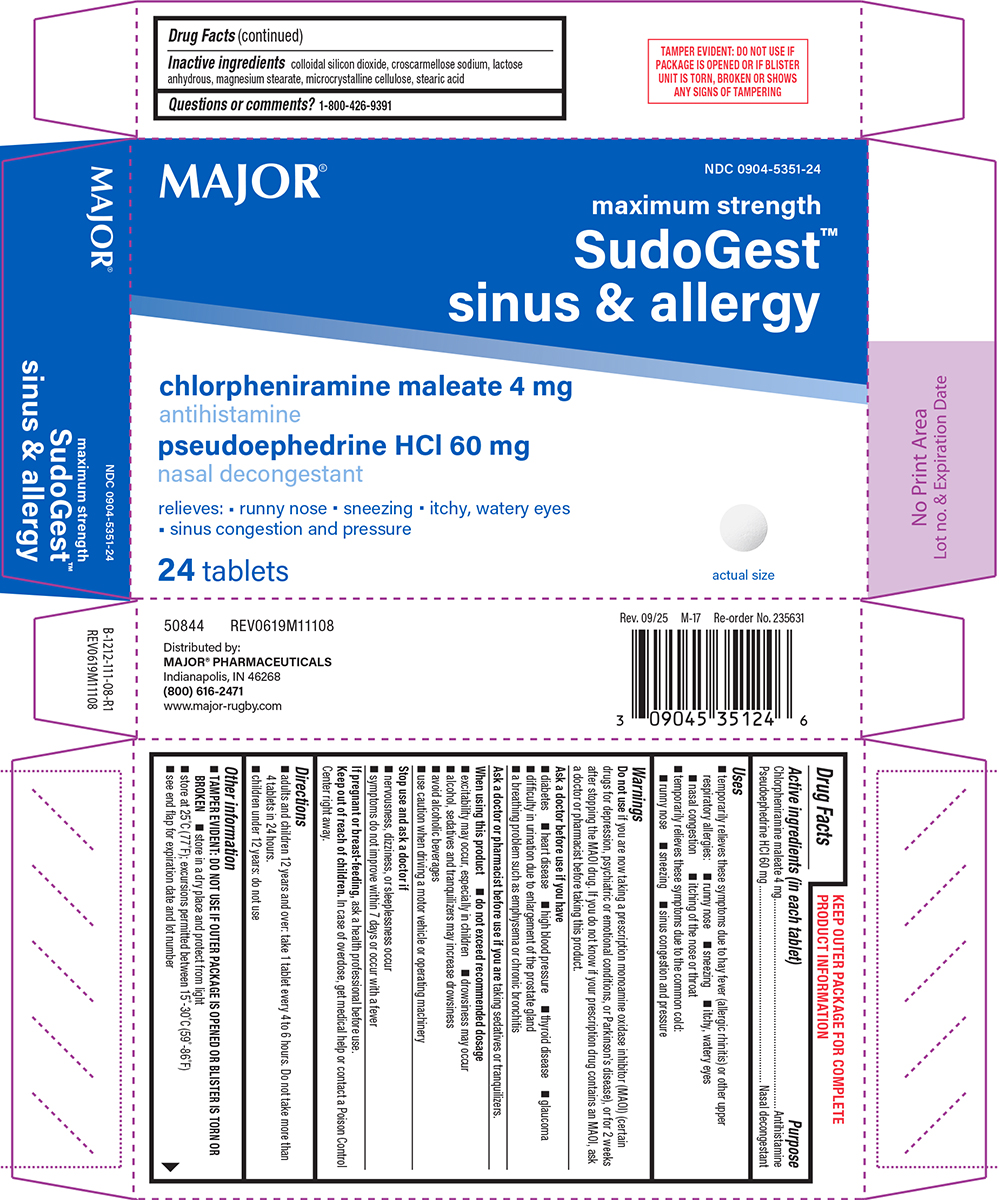 DRUG LABEL: SudoGest
NDC: 0904-5351 | Form: TABLET
Manufacturer: Major Pharmaceuticals
Category: otc | Type: HUMAN OTC DRUG LABEL
Date: 20260127

ACTIVE INGREDIENTS: CHLORPHENIRAMINE MALEATE 4 mg/1 1; PSEUDOEPHEDRINE HYDROCHLORIDE 60 mg/1 1
INACTIVE INGREDIENTS: SILICON DIOXIDE; CROSCARMELLOSE SODIUM; ANHYDROUS LACTOSE; MAGNESIUM STEARATE; MICROCRYSTALLINE CELLULOSE; STEARIC ACID

Major 44-111

Active ingredients (in each tablet)

Chlorpheniramine maleate 4 mg
Pseudoephedrine HCl 60 mg

Purpose

Antihistamine
Nasal decongestant

Uses

- temporarily relieves these symptoms due to hay fever (allergic rhinitis) or other upper respiratory allergies:
  - runny nose
  - itchy, watery eyes
  - nasal congestion
  - sneezing
  - itching of the nose or throat
- temporarily relieves these symptoms due to the common cold:
  - runny nose
  - sneezing
  - sinus congestion and pressure

Warnings

Do not use

if you are now taking a prescription monoamine oxidase inhibitor (MAOI) (certain drugs for depression, psychiatric or emotional conditions, or Parkinson's disease), or for 2 weeks after stopping the MAOI drug. If you do not know if your prescription drug contains an MAOI, ask a doctor or pharmacist before taking this product.

Ask a doctor before use if you have

- a breathing problem such as emphysema or chronic bronchitis
- heart disease
- high blood pressure
- diabetes
- glaucoma
- thyroid disease
- difficulty in urination due to enlargement of the prostate gland

Ask a doctor or pharmacist before use if you are

taking sedatives or tranquilizers.

When using this product

- do not exceed recommended dosage
- drowsiness may occur
- excitability may occur, especially in children
- alcohol, sedatives and tranquilizers may increase drowsiness
- avoid alcoholic beverages
- use caution when driving a motor vehicle or operating machinery

Stop use and ask a doctor if

- nervousness, dizziness, or sleeplessness occur
- symptoms do not improve within 7 days or occur with a fever

If pregnant or breast-feeding,

ask a health professional before use.

Keep out of reach of children.

In case of overdose, get medical help or contact a Poison Control Center right away.

Directions

- adults and children 12 years and over: take 1 tablet every 4 to 6 hours. Do not take more than 4 tablets in 24 hours.
- children under 12 years: do not use

Other information

- TAMPER EVIDENT: DO NOT USE IF OUTER PACKAGE IS OPENED OR BLISTER IS TORN OR BROKEN
- store at 25ºC (77ºF); excursions permitted between 15º-30ºC (59º-86ºF)
- store in a dry place and protect from light
- see end flap for expiration date and lot number

Inactive ingredients

colloidal silicon dioxide, croscarmellose sodium, lactose anhydrous, magnesium stearate, microcrystalline cellulose, stearic acid

Questions or comments?

1-800-426-9391

Principal Display Panel

MAJOR®

NDC 0904-5351-24

Maximum Strength
SudoGest Sinus & Allergy

chlorpheniramine maleate 4 mg
antihistamine
pseudoephedrine HCl 60 mg
nasal decongestant

relieves: • runny nose sneezing itchy, watery eyes
sinus congestion and pressure

24 Tablets

Actual Size

50844 REV0619M11108

Distributed by:
MAJOR® PHARMACEUTICALS
Indianapolis, IN 46268
(800) 616-2471
www.major-rugby.com

TAMPER EVIDENT: DO NOT USE IF
PACKAGE IS OPENED OR IF BLISTER
UNIT IS TORN, BROKEN OR SHOWS
ANY SIGNS OF TAMPERING

Major 44-111